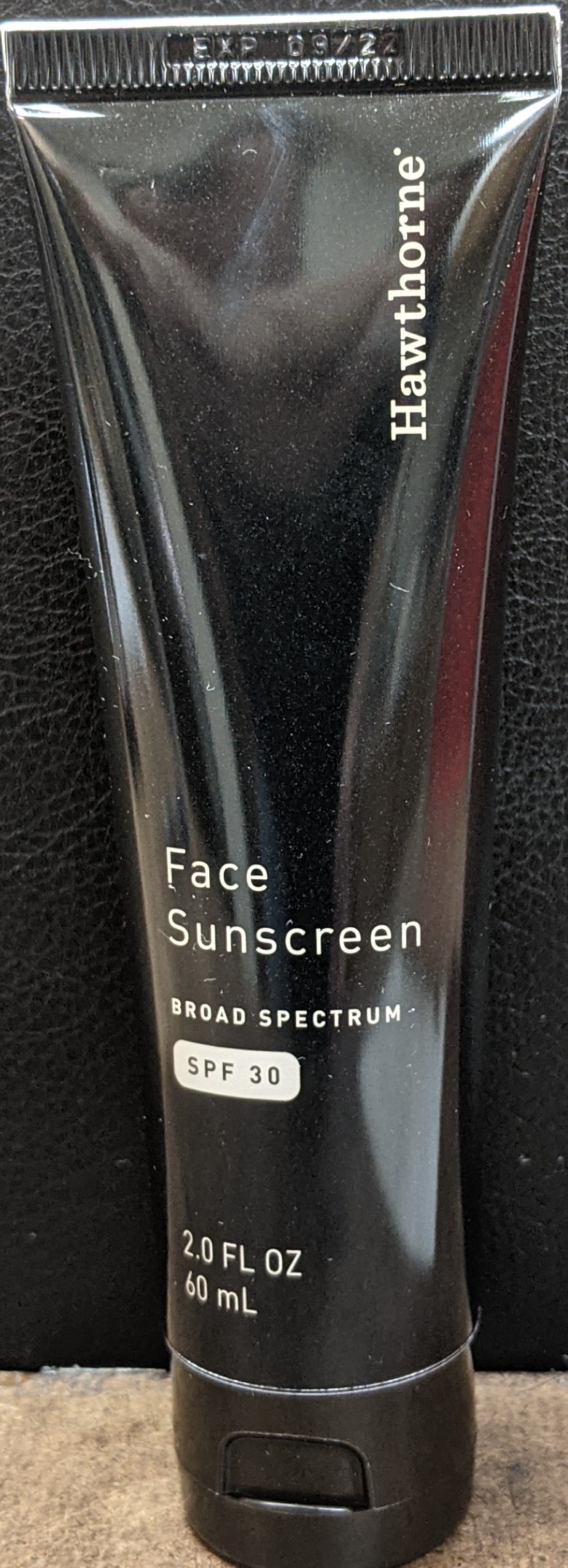 DRUG LABEL: HWT SPF 30 Unscented Face Sunscreen 2fl oz
NDC: 72496-1055 | Form: CREAM
Manufacturer: Naturich Labs, Inc
Category: otc | Type: HUMAN OTC DRUG LABEL
Date: 20210105

ACTIVE INGREDIENTS: ZINC OXIDE 11.25 g/60 g
INACTIVE INGREDIENTS: WATER 45 g/60 g

Hawthorne Face Sunscreen SPF 30

Active Ingredients

Zinc Oxide: 11.25% Purpose: Sunscreen

Titanium Dioxide: 1.50% Purpose: Sunscreen

Purpose

Sunscreen

Use

When using this product, keep out of eyes, ears, and mouth. In case of contact with eyes, rinse eyes thoroughly with water. Stop use and ask a doctor if irritation or rash occurs. These may be signs of a serious condition. Keep out of reach of children. If swallowed, get medical help or contact Poison Control Center right away.

Use

Helps prevent sunburn.

If used as directed with other sun protection measures (see Directions), decreases the risk of skin cancer and early skin aging caused by the sun.

Warnings

For external use only.

Do not use on damage or broken skin.

When using this product, keep out of eyes. Rinse with water to remove

Stop use and ask a doctor if rash occurs.

Keep out of reach of children. If swallowed, get medical help or contact a Poison Control Center immediately.

Do not use

In children less than 2 months of age.

On open skin wounds

Stop use and contact a doctor if rash occurs.

Stop Use

Stop use and ask a doctor if irritation or rash occurs. Theses may be signs of a serious condition.

Keep out of reach of children. If swallowed, get medical help of contact a Poison Control Center right away.

Directions

Apply generously 15 minutes before sun exposure.

For children under 6 months of age; Ask a doctor

Reapply at least every 2 hours

Use water-resistant sunscreen if swimming or sweating

Sun Protection Measures. Spending time in the sun increases your risk of skin cancer and early skin aging. To decrease this risk, regularly use a sunscreen with a Broad Spectrum SPF value of 15 or higher and other sun protection measures including limit time in the sun, especially from 10 a.m. -2 p.m, and wear long-sleeved shirts, pants, hats, and sunglasses.

Additional Information

Protect the product in this container from excessive heat and direct sun.

Inactive Ingredients:

Water (Aqua), Organic Aloe Barbadensis Leaf Juice, Caprylic/Capric Triglyceride, Glycerin, Cetearyl Alcohol, Coconut Alkanes, Coco-Caprylate, Cetearyl Glucoside, Cetyl Palmitate, Galactoarabinan, Rosa Centifolia Flower Extract, Lavandula Angustifolia (Lavender) Flower Extract, Camellia Sinensis (Green Tea) Leaf Extract, Sorbitan Oleate, Sorbitan Palmitate, Anhydroxylitol, Coco-Caprylate/Caprate, Xylitylglucoside, Xylitol, Glyceryl Isostearate, Polyhydroxystearic Acid, Tocopherol, Sorbitan Isostearate, Caprylyl/Capryl Glucoside, Hydroxyethyl Acrylate/ Sodium Acryloyldimethyl Taurate Copolymer, Alumina, Jojoba Esters, Phenoxyethanol, Benzyl Alcohol.